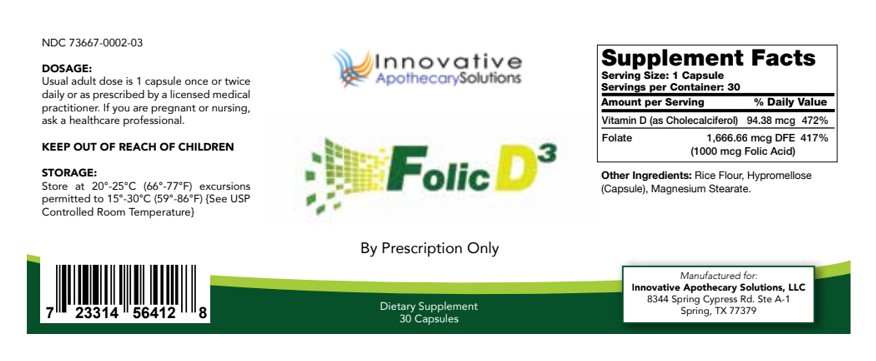 DRUG LABEL: Folic D3
NDC: 73667-002 | Form: CAPSULE
Manufacturer: Innovative Apothecary Solutions
Category: other | Type: DIETARY SUPPLEMENT
Date: 20200826

ACTIVE INGREDIENTS: FOLIC ACID 1.66 mg/1 1
INACTIVE INGREDIENTS: CHOLECALCIFEROL; MAGNESIUM STEARATE; HYPROMELLOSE, UNSPECIFIED; BROWN RICE

Folic D3

Description

Folic D3 is a dietary supplement intended for oral administration

Indication and Usage

For Prescription only

Precaution

If Pregnant or Nursing ask a healthcare professional.

Warnings

KEEP OUT OF REACH OF CHILDREN.

Storage

Store at 20 to 25°C (68 to 77°F)excursions permitted to 15°-30°C (59°-86°F) [see USP Controlled Room Temperature|

Dosage and Administration

Usual Adults does is 1 capsule once or twice daily or as prescribed by a licensed medical practitioner. If you are pregnant or nursing, as a healthcare professional.